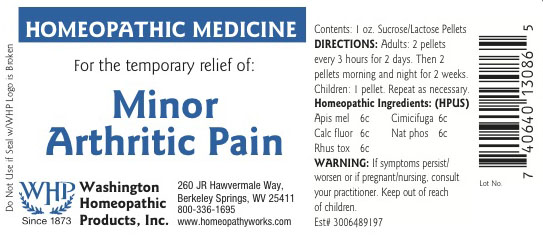 DRUG LABEL: Minor Arthritic Pain
NDC: 68428-013 | Form: PELLET
Manufacturer: Washington Homeopathic Products
Category: homeopathic | Type: HUMAN OTC DRUG LABEL
Date: 20191223

ACTIVE INGREDIENTS: APIS MELLIFERA 6 [hp_C]/28 g; BLACK COHOSH 6 [hp_C]/28 g; CALCIUM FLUORIDE 6 [hp_C]/28 g; SODIUM PHOSPHATE, DIBASIC, HEPTAHYDRATE 6 [hp_C]/28 g; TOXICODENDRON PUBESCENS LEAF 6 [hp_C]/28 g
INACTIVE INGREDIENTS: SUCROSE; LACTOSE

DRUG FACTS

ACTIVE INGREDIENTS

APIS MEL 6C

CIMICIFUGA 6C

CALC FLUOR

NAT PHOS 6C

RHUS TOX 6C

USES

To relieve the symptoms of stiffness of the joints and muscles and soreness after overexertion. Tired bruised feeling.

KEEP OUT OF REACH OF CHILDREN

Keep this and all medicines out of reach of children.

INDICATIONS

APIS MEL Stings

CIMICIFUGA Back pains

CALC FLUOR Joint pain

NAT PHOS Sour belching

RHUS TOX Better motion

STOP USE AND ASK DOCTOR

If symptoms persist/worsen or if pregnant/nursing, stop use and consult your practitioner.

DIRECTIONS

Adults 2 pellets every 3 hours for 2 days. Then 2 pellets morning and night for 2 weeks.

Children: 1 pellet. Repeat as necessary.

INACTIVE INGREDIENTS

Sucrose/Lactose

PRINCIPAL DISPLAY PANEL

Enter section text here